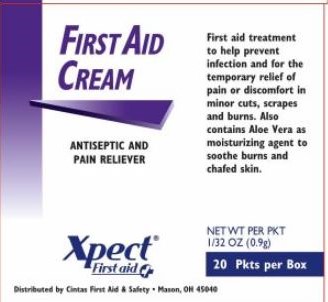 DRUG LABEL: Xpect First Aid Cream
NDC: 42961-214 | Form: CREAM
Manufacturer: Cintas Corporation
Category: otc | Type: HUMAN OTC DRUG LABEL
Date: 20250929

ACTIVE INGREDIENTS: LIDOCAINE HYDROCHLORIDE 0.5 g/100 g; BENZALKONIUM CHLORIDE 0.13 g/100 g
INACTIVE INGREDIENTS: aloe; CETYL ALCOHOL; DIAZOLIDINYL UREA; EDETATE DISODIUM; GLYCERIN; GLYCERYL MONOSTEARATE; METHYLPARABEN; MINERAL OIL; POLYETHYLENE GLYCOL, UNSPECIFIED; PROPYLENE GLYCOL; PROPYLPARABEN; WATER; STEARIC ACID; TROLAMINE

Xpect First Aid Cream

Active ingredients (in each packet)

- Benzalkonium chloride 0.13%

- Lidocaine HCL 0.5%

Purpose

- first aid antiseptic

- external analgesic

Uses

first aid to help prevent infection and for the temporary relief of pain in minor cuts, scrapes, and burns

Warnings

For external use only

Do not use

- in the eyes or apply over large areas of the body
- longer than 1 week unless directed by a doctor
- in large quantities, particularly over raw surfaces or blistered areas

Ask a doctor before use if you have

- deep or puncture wounds
- animal bites
- serious burns

Stop use and ask a doctor if

conditions persists or gets worse

- symptoms persists for more than 7 days
- condition clears up and occurs again within a few days
- a rash or other allergic reaction develops

Keep out of reach of children.

If swallowed, get medical help or contact a Poison Control Center right away.

Directions

adults and children 2 years of age and older

- clean the affected area
- may be covered with a sterile bandage
- apply a small amount (an amount equal to the surface area of the tip of finger) 1 to 3 times daily

Other information

- do not use if packet is torn, cut or opened
- store at room temperature (do not freeze)
- see packet for Lot Number and expiration date

Inactive ingredients

aloe vera, cetyl alcohol, diazolidinyl urea, edetate disodium, glycerin, glyceryl monostearate, methylparaben, mineral oil, polyethylene glycol, propylene glycol, propylparaben, purified water, stearic acid, trolamine

Questions?

1-800-973-2811

Principal Display Panel Box

FIRST AID CREAM

ANTISEPTIC AND PAIN RELIEVER

First aid treatment to help prevent infection and for the temporary relief of pain or discomfort in minor cuts, scrapes and burns. Also contains Aloe Vera as moisturizing agent to soothe burns and chafed skin.

XPECT® First aid

Distributed by Cintas First Aid & Safety • Mason, OH 45040

NET WT PER PKT

1/32 OZ (0.9g)

20 Pkts per Box